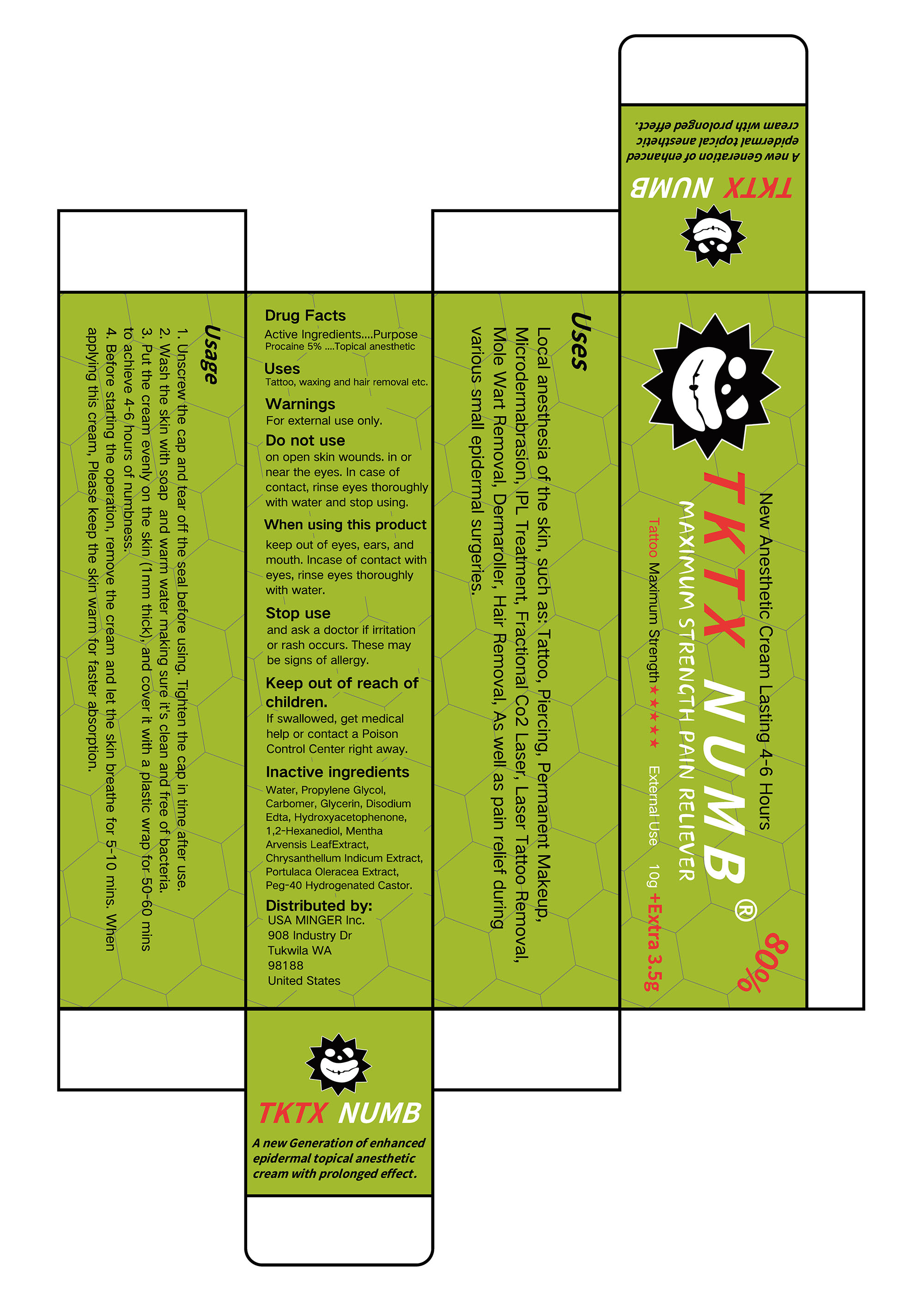 DRUG LABEL: TKTX NUMB
NDC: 84353-004 | Form: OINTMENT
Manufacturer: USA MINGER Inc.
Category: otc | Type: HUMAN OTC DRUG LABEL
Date: 20250319

ACTIVE INGREDIENTS: PROCAINE 5 g/100 g
INACTIVE INGREDIENTS: WATER; PURSLANE; CHRYSANTHELLUM INDICUM TOP; HYDROXYACETOPHENONE; GLYCERIN; CARBOMER; PROPYLENE GLYCOL; 1,2-HEXANEDIOL; EDETATE DISODIUM; MENTHA ARVENSIS LEAF; PEG-40 HYDROGENATED CASTOR OIL

TKTX NUMB

ACTIVE INGREDIENT

Procaine 5%

PURPOSE

Topical anesthetic

INDICATIONS AND USAGE

Tattoo, waxing and hair removal etc.

WARNINGS

For external use only.

DO NOT USE

on open skin wounds. in ornear the eyes. in case of contact, rinse eyes thoroughlywith water and stop using.

WHEN USING

keep out of eyes, ears, andmouth. Incase of contact witheyes, rinse eyes thoroughly with water.

STOP USE

and ask a doctor if irritationor rash occurs. These may be signs of allergy.

KEEP OUT OF REACH OF CHILDREN

If swallowed, get medicalhelp or contact a Poison Control Center right away.

DOSAGE AND ADMINISTRATION

1. Wnscrew the cap and tear off the seal before using, Tighten the cap in time after use.
2. Wash the skin with soap and warm water making sure it's clean and free of bacteria.
3. Put the cream evenly on the skin (1 mm thick), and cover it with a plastic wrap for 50-60 minsto achieve 4-6 hours of numbness.
4. Before starting the operation, remove the cream and let the skin breathe for 5-10 mins. Whenapplving this cream, Please keep the skin warm for faster absorption.

INACTIVE INGREDIENT

WATER
PROPYLENE GLYCOL
CARBOMER
GLYCERIN
DISODIUM EDTA
HYDROXYACETOPHENONE

1,2-HEXANEDIOL
MENTHA ARVENSIS LEAF EXTRACT
CHRYSANTHELLUM INDICUM EXTRACT
PORTULACA OLERACEA EXTRACT
PEG-40 HYDROGENATED CASTOR